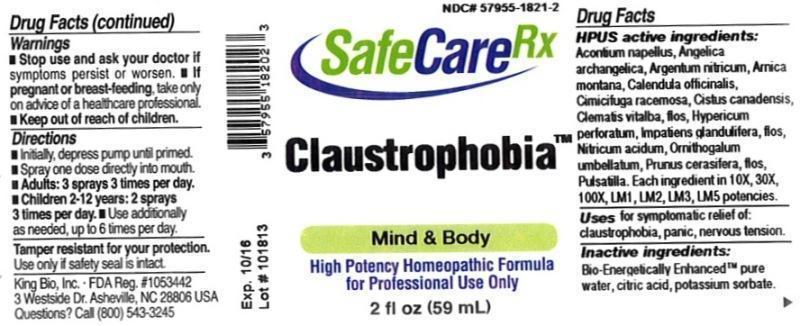 DRUG LABEL: Claustrophobia
NDC: 57955-1821 | Form: LIQUID
Manufacturer: King Bio Inc.
Category: homeopathic | Type: HUMAN OTC DRUG LABEL
Date: 20131210

ACTIVE INGREDIENTS: ACONITUM NAPELLUS 10 [hp_X]/59 mL; ANGELICA ARCHANGELICA ROOT 10 [hp_X]/59 mL; SILVER NITRATE 10 [hp_X]/59 mL; ARNICA MONTANA 10 [hp_X]/59 mL; CALENDULA OFFICINALIS FLOWERING TOP 10 [hp_X]/59 mL; BLACK COHOSH 10 [hp_X]/59 mL; HELIANTHEMUM CANADENSE 10 [hp_X]/59 mL; CLEMATIS VITALBA FLOWER 10 [hp_X]/59 mL; HYPERICUM PERFORATUM 10 [hp_X]/59 mL; IMPATIENS GLANDULIFERA FLOWER 10 [hp_X]/59 mL; NITRIC ACID 10 [hp_X]/59 mL; ORNITHOGALUM UMBELLATUM 10 [hp_X]/59 mL; PRUNUS CERASIFERA FLOWER 10 [hp_X]/59 mL; PULSATILLA VULGARIS 10 [hp_X]/59 mL
INACTIVE INGREDIENTS: WATER; CITRIC ACID MONOHYDRATE; POTASSIUM SORBATE

Claustrophobia

Drug Facts

____________________________________________________________________________________________________________________

HPUS active ingredients: Aconitum napellus, Angelica archangelica, Argentum nitricum, Arnica montana, Calendula officinalis, Cimicifuga racemosa, Cistus canadensis, Clematis vitalba, flos, Hypericum perforatum, Impatiens glandulifera, flos, Nitricum acidum, Ornithogalum umbellatum, Prunus cerasifera, flos, Pulsatilla. Equal volumes of each ingredient in 10X, 30X, 100X, LM1, LM2, LM3, LM5 potencies.

INDICATIONS AND USAGE

Uses for symptomatic relief of: claustrophobia, panic, nervous tension.

INACTIVE INGREDIENT

Inactive ingredients: Bio-Energetically Enhanced pure water, citric acid, potassium sorbate.

Warnings

- Stop use and ask your doctor if symptoms persist or worsen.
- If pregnant or breast-feeding, take only on advice of a healthcare professional.

- Keep out of reach of children.

Directions:

- Initially, depress pump until primed.
- Spray one dose directly into mouth.
- Adults: 3 sprays 3 times per day.
- Children 2-12 years: 2 sprays 3 times per day.
- Use additionally as needed, up to 6 times per day.

OTHER SAFETY INFORMATION

Tamper resistant for your protection. Use only if safety seal is intact.

PURPOSE

Uses for symptomatic relief of:

- claustrophobia
- panic
- nervous tension